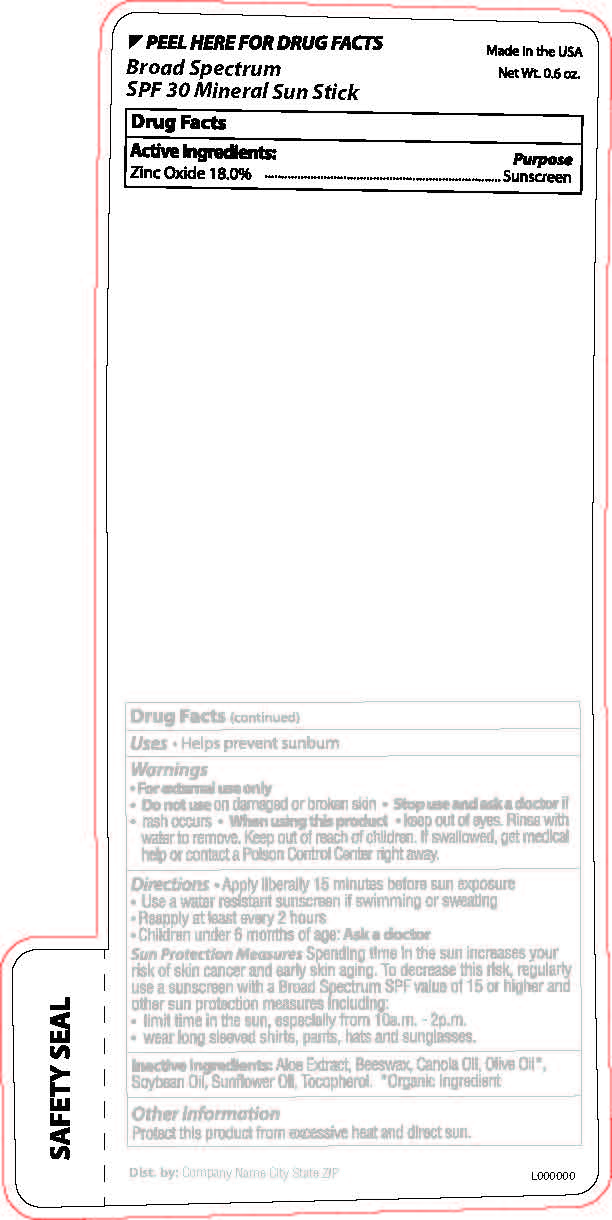 DRUG LABEL: Broad Spectrum SPF 30 Mineral Sun Stick
NDC: 65692-0565 | Form: STICK
Manufacturer: Raining Rose
Category: otc | Type: HUMAN OTC DRUG LABEL
Date: 20231018

ACTIVE INGREDIENTS: ZINC OXIDE 3.06 g/17 g
INACTIVE INGREDIENTS: OLIVE OIL; CANOLA OIL; SOYBEAN OIL; TOCOPHEROL; ALOE VERA LEAF; SUNFLOWER OIL; WHITE WAX

Broad Spectrum SPF 30 Mineral Sun Stick

ACTIVE INGREDIENT

Zinc Oxide 18%

PURPOSE

Sunscreen

INDICATIONS AND USAGE

Helps prevent sunburn

WARNINGS

For external use only. Do not use on damaged or broken skin. Stop use and ask a doctor if rash occurs. When using this product keep out of eyes. Rinse with water to remove.

Keep out of reach of children. If swallowed, get medical help or contact a Poison control Center right away.

DOSAGE AND ADMINISTRATION

Apply liberally 15 minutes before sun exposure. Use a water resistant sunscreen if swimming or sweating. Reapply at least every 3 hours. Children under 8 months of age: Ask a doctor.

Sun Protection Measures. Spending time in the sun increases your risk of skin cancer and early skin aging. To decrease this risk, regularly use a sunscreen with a Broad Spectrum SPF value of 15 or higher and other sun protection measures including: limit time in the sun, especially from 10am-2pm. Wear long sleeved shirts, pants, hats and sunglasses.

OTHER SAFETY INFORMATION

Protect this product from excessive heat and direct sun.

INACTIVE INGREDIENT

Aloe Extract, Beeswax, Canola Oil, Olive Oil*, Soybean Oil, Sunflower Oil, Tocopherol. *Organic Ingredient

INDICATIONS AND USAGE

Helps prevent sunburn

DOSAGE AND ADMINISTRATION

Apply liberally 15 minutes before sun exposure